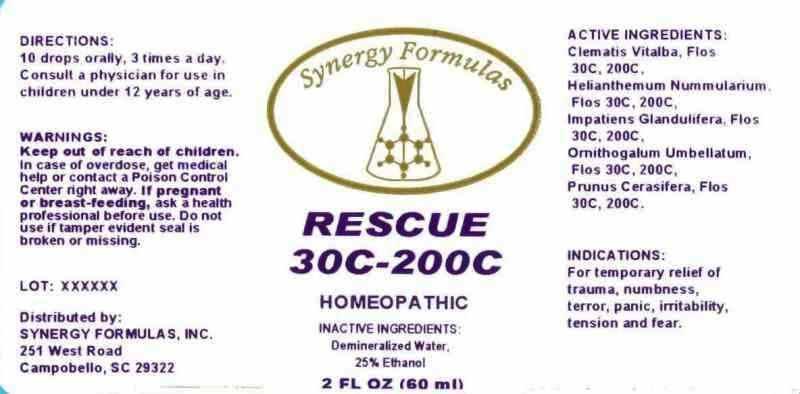 DRUG LABEL: Rescue
NDC: 43772-0023 | Form: LIQUID
Manufacturer: Synergy Formulas, Inc.
Category: homeopathic | Type: HUMAN OTC DRUG LABEL
Date: 20140612

ACTIVE INGREDIENTS: CLEMATIS VITALBA FLOWER 30 [hp_C]/1 mL; HELIANTHEMUM NUMMULARIUM FLOWER 30 [hp_C]/1 mL; IMPATIENS GLANDULIFERA FLOWER 30 [hp_C]/1 mL; ORNITHOGALUM UMBELLATUM FLOWERING TOP 30 [hp_C]/1 mL; PRUNUS CERASIFERA FLOWER 30 [hp_C]/1 mL
INACTIVE INGREDIENTS: WATER; ALCOHOL

DRUG FACTS:

ACTIVE INGREDIENTS:

Clematis Vitalba, Flos 30C, 200C, Helianthemum Nummularium, Flos 30C, 200C, Impatiens Glandulifera, Flos 30C, 200C, Ornithogalum Umbellatum, Flos 30C, 200C, Prunus Cerasifera, Flos 30C, 200C

INDICATIONS:

For temporary relief of trauma, numbness, terror, panic, irritability, tension and fear.

WARNINGS:

Keep out of reach of children. In case of overdose, get medical help or contact a Poison Control Center right away.

If pregnant or breast-feeding, ask a health care professional before use.

Do not use if tamper evident seal is broken or missing.

Keep out of reach of children. In case of overdose, get medical help or contact a Poison Control Center right away.

DIRECTIONS:

10 drops orally, 3 times a day. Consult a physician for use in children under 12 years of age.

INDICATIONS:

For temporary relief of trauma, numbness, terror, panic, irritability, tension and fear.

INACTIVE INGREDIENTS:

Demineralized Water, 25% Ethanol

QUESTIONS:

Distributed by:

SYNERGY FORMULAS, INC.

251 West Road

Campobello, SC 29322

PACKAGE DISPLAY LABEL:

Synergy Formulas

RESCUE

30C-200C

HOMEOPATHIC

2 FL OZ (60 ml)